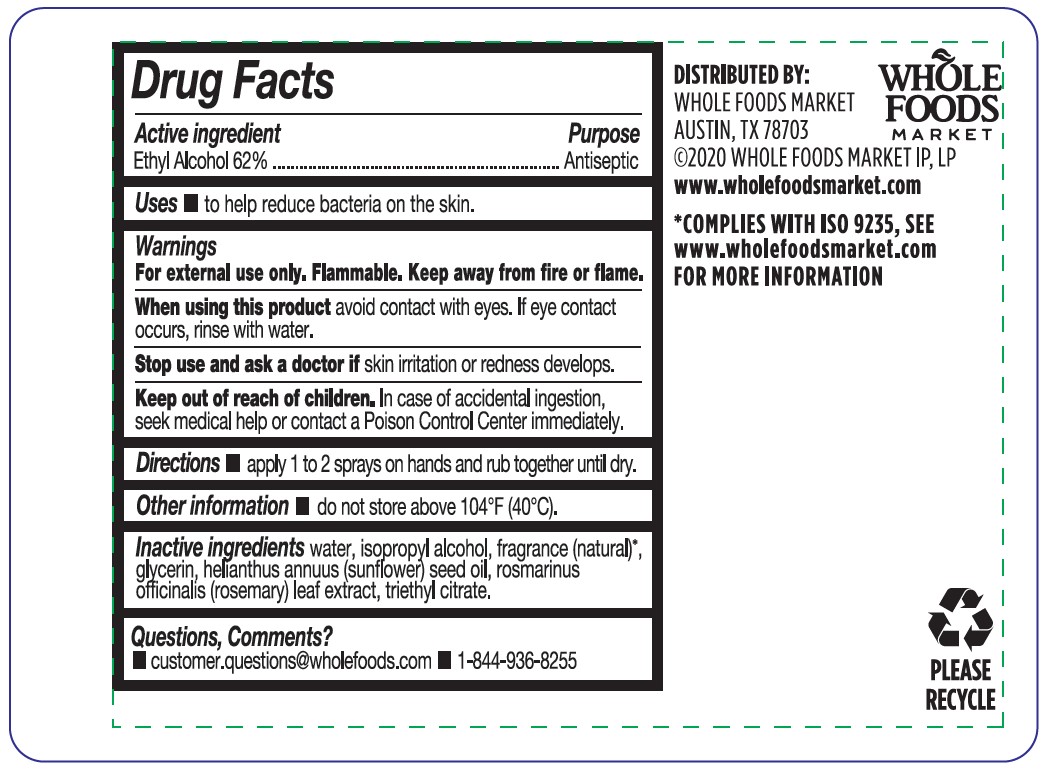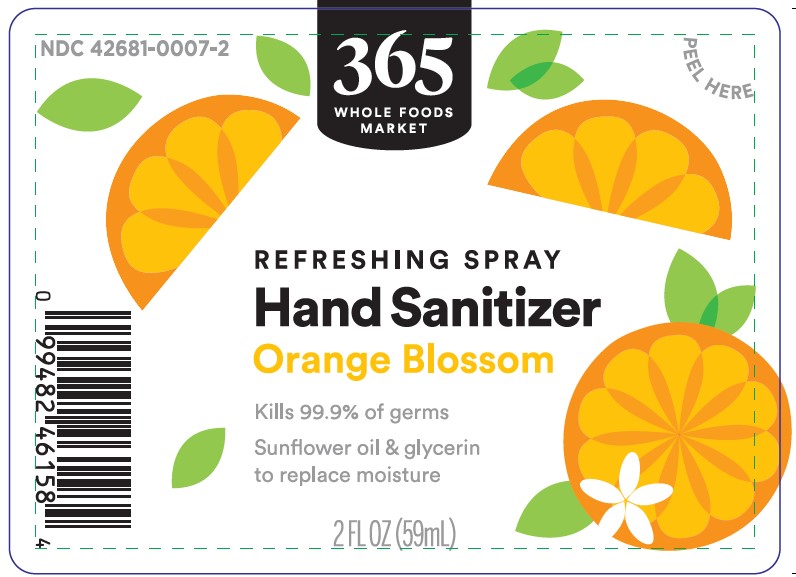 DRUG LABEL: Hand Sanitizer
NDC: 42681-0007 | Form: SPRAY
Manufacturer: Whole Foods Market, Inc.
Category: otc | Type: HUMAN OTC DRUG LABEL
Date: 20241102

ACTIVE INGREDIENTS: ALCOHOL 62 mL/100 mL
INACTIVE INGREDIENTS: WATER; ISOPROPYL ALCOHOL; GLYCERIN; SUNFLOWER OIL; ROSEMARY; TRIETHYL CITRATE

Whole Foods 365 Hand Sanitizer Spray - Orange Blossom 2 fl oz

Active ingredient Purpose
Ethyl Alcohol 62% Antiseptic

PURPOSE

Uses ■ to help reduce bacteria on the skin.

WARNINGS

For external use only. Flammable. Keep away from fire or flame.

When using this product avoid contact with eyes. If eye contact occurs, rinse with water.

Stop use and ask a doctor if skin irritation or redness develops.

Keep out of reach of children. In case of accidental ingestion, seek medical help or contact a Poison Control Center immediately.

DOSAGE AND ADMINISTRATION

Directions ■ apply 1 to 2 sprays on hands and rub together until dry

STORAGE AND HANDLING

Do not store above 104F (40C)

INACTIVE INGREDIENT

Inactive ingredients water, isopropyl alcohol, fragrance (natural)*, glycerin, helianthus annuus (sunflower) seed oil, rosmarinus
officinalis (rosemary) leaf extract, triethyl citrate.

QUESTIONS

Questions, Comments? ■ customer.questions@wholefoods.com ■ 1-844-936-8255